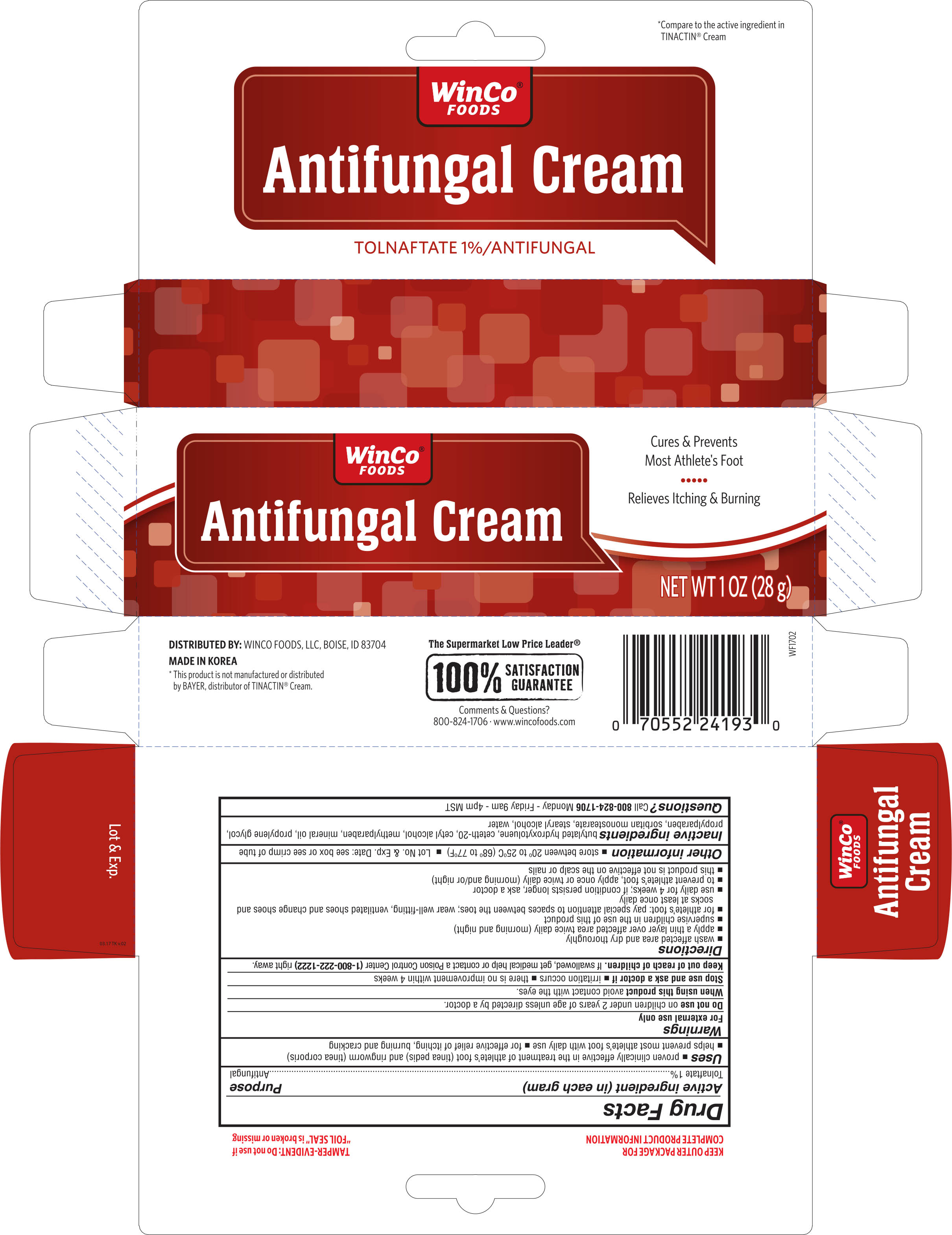 DRUG LABEL: Winco Foods Tolnaftate
NDC: 67091-276 | Form: CREAM
Manufacturer: Winco Foods, LLC
Category: otc | Type: HUMAN OTC DRUG LABEL
Date: 20251023

ACTIVE INGREDIENTS: TOLNAFTATE 10 mg/1 g
INACTIVE INGREDIENTS: CETETH-20; CETYL ALCOHOL; METHYLPARABEN; MINERAL OIL; PROPYLENE GLYCOL; PROPYLPARABEN; SORBITAN MONOSTEARATE; STEARYL ALCOHOL; WATER

Winco Antifungal Tolnaftate 1% Cream 1 oz (24193, 2018)

Active ingredient (in each gram) Purpose

Tolnaftate 1%--------------------------------------------------------------------------------- Antifungal

Uses

- Proven clinically effective in the treatment of athlete's foot (tinea pedis) and rignworm (tinea corporis)
- Helps prevent most athlete's foot with daily use
- For effective relief of itching, burning and cracking

Warnings:

For external use only

Do not use on children under 2 years of age unless directed by a doctor

When using this product

Avoid contact with the eyes.

Stop use and ask a doctor if

- irritation occurs
- there is no improvement within 4 weeks

Keep out of reach of children

If swallowed, get medical help or contact a Poison Control Center right away.

Directions

- wash affected area and dry thoroguhly
- apply a thin layer over affected area twice daily (morning and night)
- supervise children in the use of this product
- for athlete's foot, pay special attention to spaces between the toes, wear well-fitting, ventilated shoes and change shoes and socks at least once daily
- use daily for 4 weeks; if condition persists longer, ask a doctor
- to prevent athlete's foot, apply once or twice daily (morning and/or night)
- this product is not effective on the scalp or nails

Other information

- store between 20° to 25C° (68° to 77F°)
- Lot No & Exp. Date: see box or see crimp of tube

Inactive ingredients

buylated hydroxytoluene, ceteth-20, cetyl alcohol, methylparaben, mineral oil, propylene glycol, propylparaben, sorbitan monostearate, stearyl alcohol, water

DOSAGE AND ADMINISTRATION

DISTRIBUTED BY:

WINCO FOODS, LLC,

BOISE, ID 83704

MADE IN KOREA